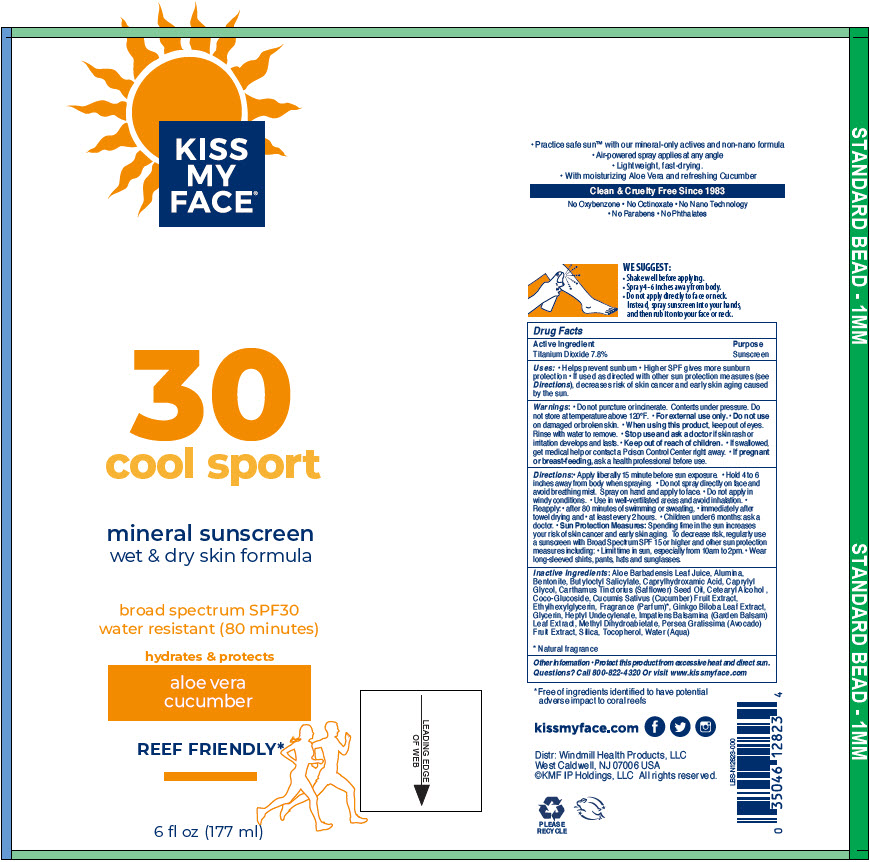 DRUG LABEL: Kiss My Face Cool Sport 30 Mineral Sunscreen
NDC: 74154-016 | Form: SPRAY
Manufacturer: Windmill Health Products, LLC
Category: otc | Type: HUMAN OTC DRUG LABEL
Date: 20220217

ACTIVE INGREDIENTS: Titanium Dioxide 78 mg/1 mL
INACTIVE INGREDIENTS: Aloe Vera Leaf; ALUMINUM OXIDE; BENTONITE; Butyloctyl Salicylate; Caprylhydroxamic Acid; Caprylyl Glycol; SAFFLOWER OIL; CETOSTEARYL ALCOHOL; Coco Glucoside; Cucumber; Ethylhexylglycerin; GINKGO; Glycerin; Heptyl Undecylenate; Impatiens Balsamina Leaf; Methyl Dihydroabietate; Avocado; SILICON DIOXIDE; Tocopherol; Water

Kiss My Face® Cool Sport 30 Mineral Sunscreen

Drug Facts

Active Ingredient

Titanium Dioxide 7.8%

Purpose

Sunscreen

Uses

- Helps prevent sunburn
- Higher SPF gives more sunburn protection
- If used as directed with other sun protection measures (see Directions), decreases risk of skin cancer and early skin aging caused by the sun.

Warnings

- Do not puncture or incinerate. Contents under pressure. Do not store at temperature above 120°F.
- For external use only.
- Do not use on damaged or broken skin.
- When using this product, keep out of eyes. Rinse with water to remove.
- Stop use and ask a doctor if skin rash or irritation develops and lasts.

- Keep out of reach of children.
- If swallowed, get medical help or contact a Poison Control Center right away.
- If pregnant or breast-feeding, ask a health professional before use.

Directions

- Apply liberally 15 minute before sun exposure.
- Hold 4 to 6 inches away from body when spraying.
- Do not spray directly on face and avoid breathing mist. Spray on hand and apply to face.
- Do not apply in windy conditions.
- Use in well-ventilated areas and avoid inhalation.
- Reapply:
  - after 80 minutes of swimming or sweating,
  - immediately after towel drying and
  - at least every 2 hours.
- Children under 6 months: ask a doctor.
- Sun Protection Measures: Spending time in the sun increases your risk of skin cancer and early skin aging. To decrease risk, regularly use a sunscreen with Broad Spectrum SPF 15 or higher and other sun protection measures including:
  - Limit time in sun, especially from 10am to 2pm.
  - Wear long-sleeved shirts, pants, hats and sunglasses.

Inactive Ingredients

Aloe Barbadensis Leaf Juice, Alumina, Bentonite, Butyloctyl Salicylate, Caprylhydroxamic Acid, Caprylyl Glycol, Carthamus Tinctorius (Safflower) Seed Oil, Cetearyl Alcohol , Coco-Glucoside, Cucumis Sativus (Cucumber) Fruit Extract, Ethylhexylglycerin, Fragrance (Parfum) [Natural fragrance] , Ginkgo Biloba Leaf Extract, Glycerin, Heptyl Undecylenate, Impatiens Balsamina (Garden Balsam) Leaf Extract, Methyl Dihydroabietate, Persea Gratissima (Avocado) Fruit Extract, Silica, Tocopherol, Water (Aqua)

Other Information

- Protect this product from excessive heat and direct sun.

Questions?

Call 800-822-4320 Or visit www.kissmyface.com

PRINCIPAL DISPLAY PANEL - 177 ml Can Label

KISS
MY
FACE®

30
cool sport

mineral sunscreen
wet & dry skin formula

broad spectrum SPF30
water resistant (80 minutes)

hydrates & protects

aloe vera
cucumber

REEF FRIENDLY*

6 fl oz (177 ml)